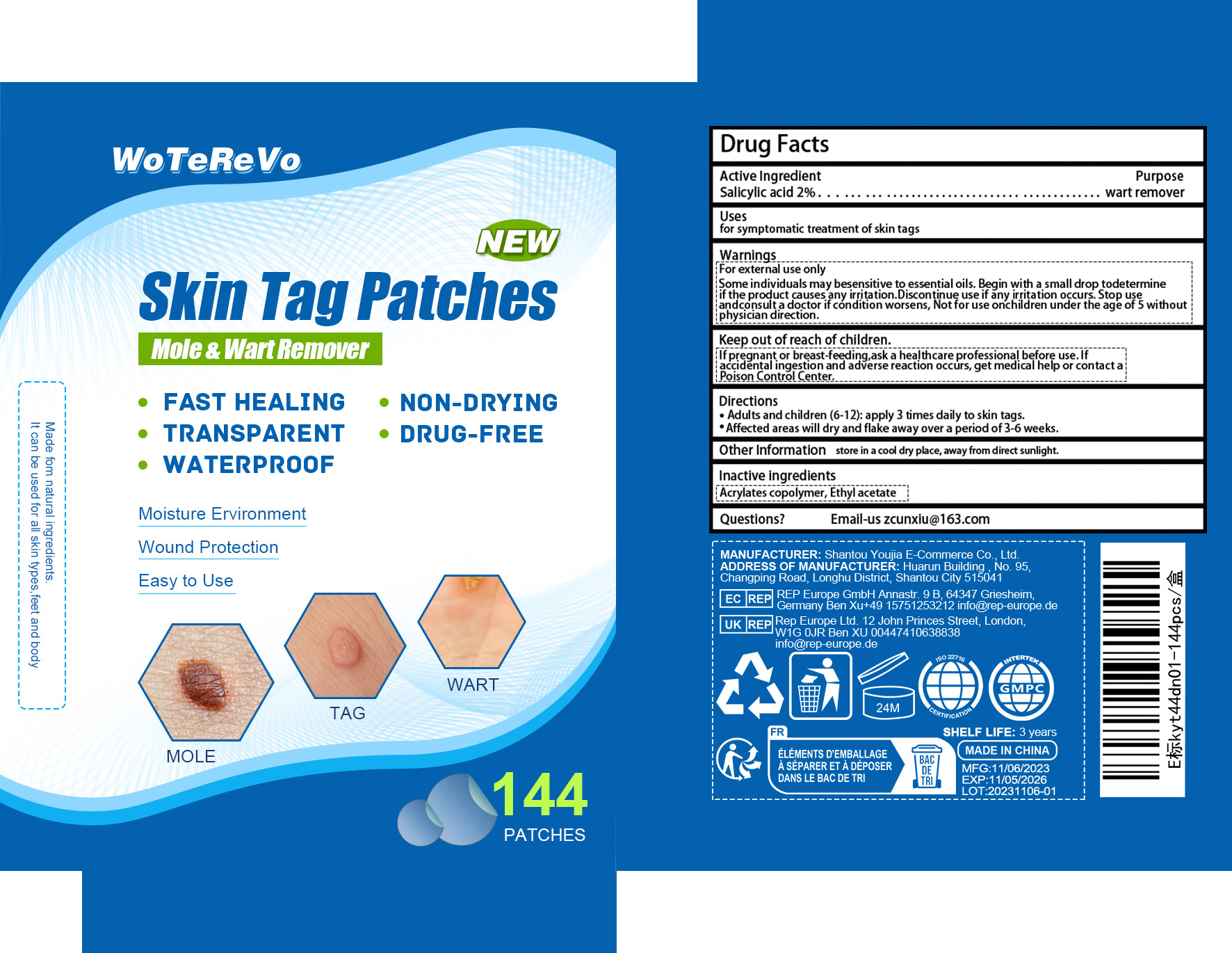 DRUG LABEL: Skin Tag Patches
NDC: 84288-002 | Form: PATCH
Manufacturer: Dongkou County Hecheng Network Technology Co., Ltd.
Category: otc | Type: HUMAN OTC DRUG LABEL
Date: 20240618

ACTIVE INGREDIENTS: SALICYLIC ACID 2 g/100 1
INACTIVE INGREDIENTS: REHMANNIA GLUTINOSA ROOT; CAMELLIA SINENSIS SEED OIL; CENTELLA ASIATICA TRITERPENOIDS; TOCOPHEROL; HYALURONIC ACID

Skin Tag Patches

ACTIVE INGREDIENT

SALICYLIC ACID 2%

PURPOSE

wart remover

Please keep out of reach of children.

INDICATIONS AND USAGE

for symptomatic treatment of skin tags

WARNINGS

Please keep out of reach of children
For external use only.
Please clean your hands before use to ensure the best results from the product.
Discontinue use if signs ofirritation or rash occur.
Store in a cool and dry place

DOSAGE AND ADMINISTRATION

1.Clean the area of skin tag and dry well.
2.Apply skin tag on desired area.
3.Leave it for a few hours or overnight
4.Replace the kin tag removal patches when it dries completely

STORAGE AND HANDLING

Store in a cool and dry place.
SHELF LIFE: 3 years

INACTIVE INGREDIENT

Camellia Sinensis Seed Oil
Rehmannia Glutinosa Extract
Tocopherol
Centella Asiatica Extract
Hyaluronic Acid